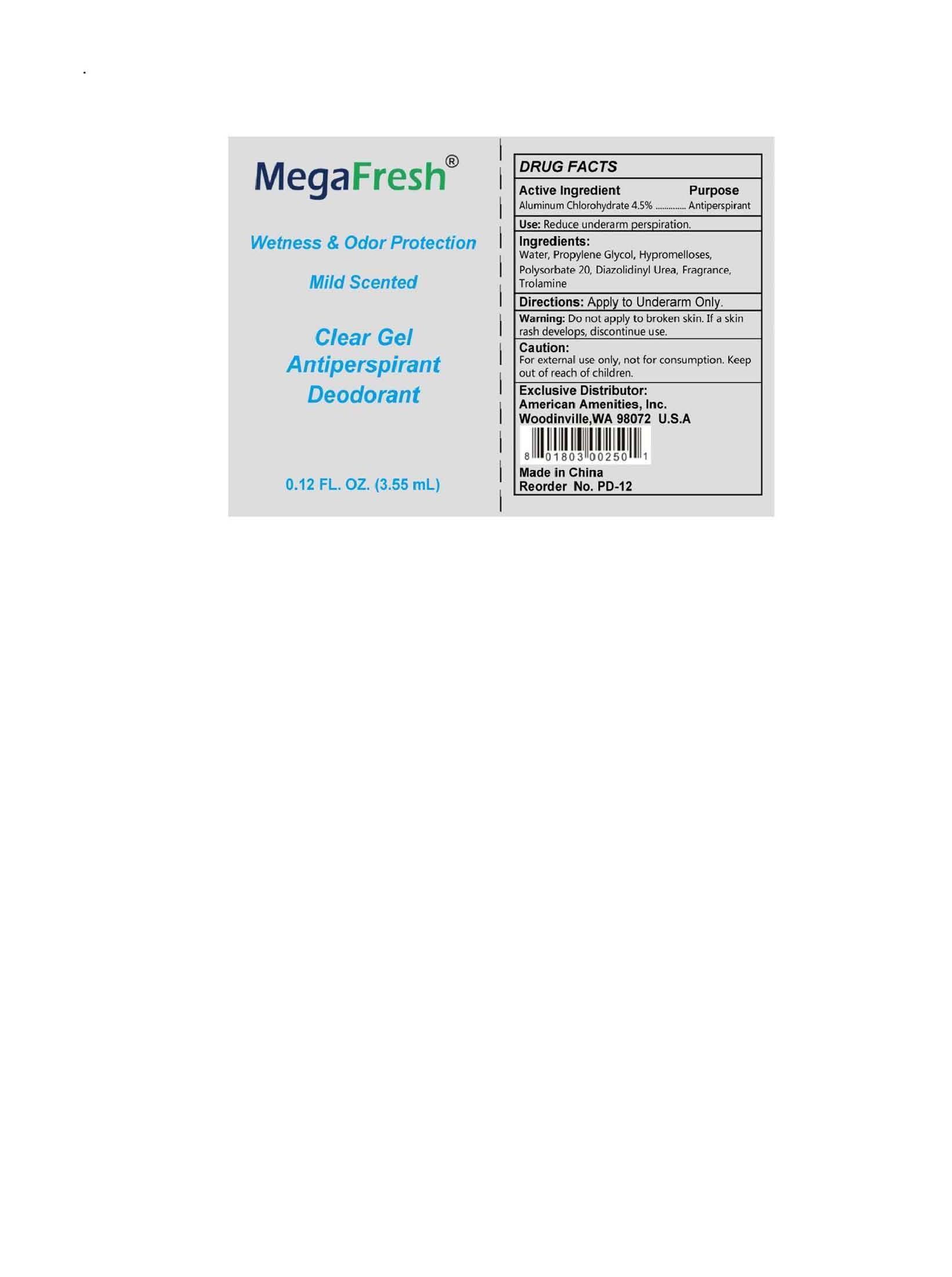 DRUG LABEL: MegaFresh Clear Gel Antiperspirant Deodorant
NDC: 54157-106 | Form: LIQUID
Manufacturer: American Amenities, Inc.
Category: otc | Type: HUMAN OTC DRUG LABEL
Date: 20141109

ACTIVE INGREDIENTS: ALUMINUM CHLOROHYDRATE 4.5 g/100 mL
INACTIVE INGREDIENTS: WATER 4.5 g/100 mL; PROPYLENE GLYCOL; TROLAMINE; HYPROMELLOSES; POLYSORBATE 20; DIAZOLIDINYL UREA

Drug Fact

Active Ingredient

Aluminum Chlorohydrate 4.5%

Purpose

Antiperspirant

Uses

Reduce underarm perspiration

Warnings:

Do not apply to broken skin

If a skin rash develops, discontinue use.

For external use only, not for consumption

Keep out of reach of children.

Directions

Apply to Underarm Only

Inactive Ingredient:

Water, Propylene Glycol, Hypromelloses, Polysorbate 20, Diazolidinyl Urea, Fragrance, Trolamine